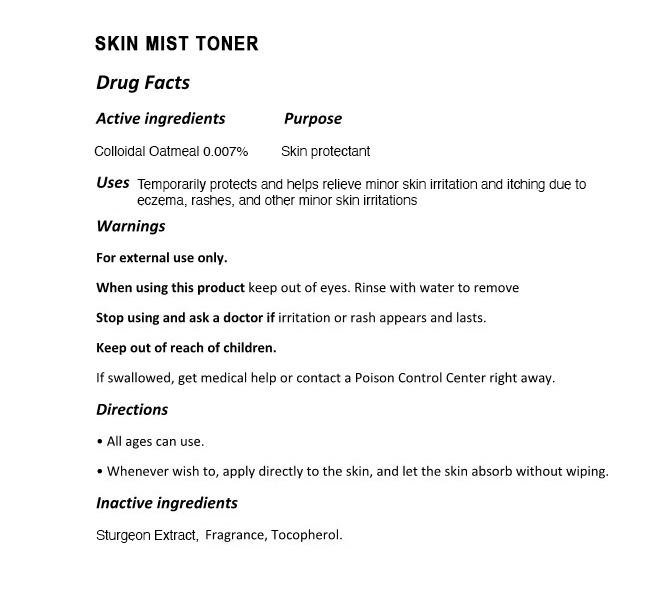 DRUG LABEL: The Zoeun Skin Mist Toner
NDC: 83636-113 | Form: SPRAY
Manufacturer: Sturgeonbio Co.,Ltd.
Category: otc | Type: HUMAN OTC DRUG LABEL
Date: 20251001

ACTIVE INGREDIENTS: OATMEAL 0.007 g/100 mL
INACTIVE INGREDIENTS: STURGEON, UNSPECIFIED; FRAGRANCE 13576; TOCOPHEROL

113 THE ZOEUN SKIN MIST TONER

Active Ingredients

Colloidal Oatmeal 0.007%

Purpose

Skin Protectant

Uses

Temporarily protects and helps relieve minor skin irritation and itching due to eczema, rashes, insect bites, and other minor skin irritations.

Warnings

Keep out of reach of children.
If swallowed, get medical help or contact a Poison Control Center right away.

Warnings

Stop using and ask a doctor if irritation or rash appears and lasts.

Warnings

When using this product keep out of eyes. Rinse with water to remove.

Warnings

For external use only.

Directions

• All ages can use.
• Whenever wish to, apply directly to the skin, and let the skin absorb without wiping.

Inactive Ingredients

Sturgeon Extract, Fragrance, Tocopherol.